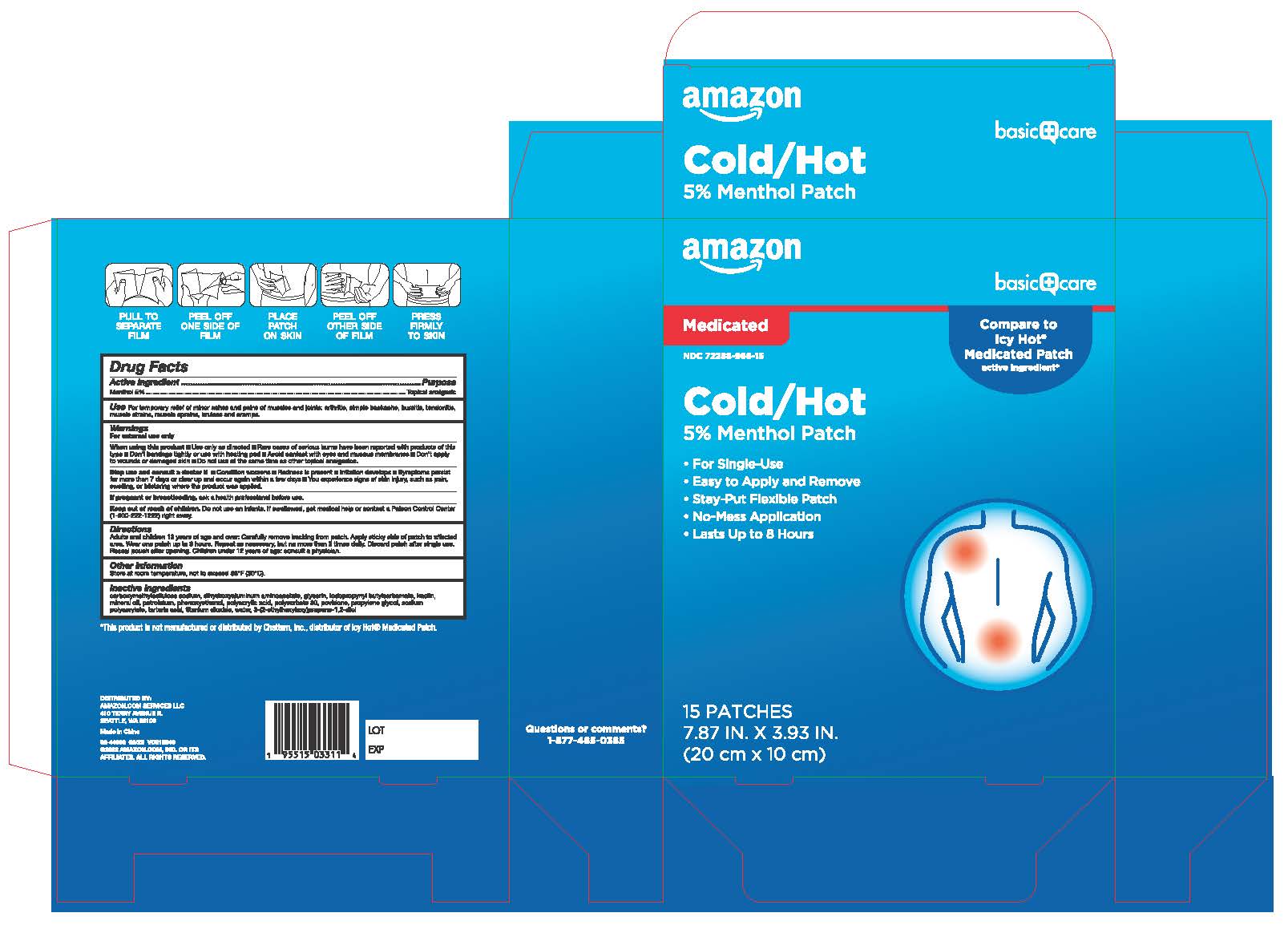 DRUG LABEL: Amazon Basics Cold and Hot Medicated Patch
NDC: 72288-966 | Form: PATCH
Manufacturer: Amazon.com Services LLC
Category: otc | Type: HUMAN OTC DRUG LABEL
Date: 20251228

ACTIVE INGREDIENTS: MENTHOL 5 g/100 g
INACTIVE INGREDIENTS: PHENOXYETHANOL; WATER; POLYACRYLIC ACID (8000 MW); PETROLATUM; CARBOXYMETHYLCELLULOSE SODIUM, UNSPECIFIED FORM; POVIDONE; POLYETHYLENE GLYCOL 400; IODOPROPYNYL BUTYLCARBAMATE; KAOLIN; POLYSORBATE 80; ETHYLHEXYLGLYCERIN; DIHYDROXYALUMINUM AMINOACETATE; TITANIUM DIOXIDE; GLYCERIN; SODIUM POLYACRYLATE (8000 MW); TARTARIC ACID

Amazon Basics Cold & Hot Medicated Patch

Active Ingredient

Menthol 5%

Purpose

Topical analgesic

Use

For temporary relief of minor aches and pains of muscles and joints: arthritis, simple backache, bursitis, tendonitis, muscle strains, muscle sprains, bruises and cramps.

Warnings

For external use only

When using this product

■Use only as directed ■ Rare cases of serious burns have been reported with products of this type ■Don't bandage tightly or use with heating pad ■ Avoid contact with eyes and mucous membranes ■Don't apply to wounds or damaged skin ■ Do not use at the same time as other topical analgesics.

Stop use and consult a doctor if

■Condition worsens ■ Redness is present ■Irritation develops ■ Symptoms persist for more than 7 days or clear up and occur again within a few days ■ You experience signs of skin injury, such as pain, swelling, or blistering where the product was applied.

If pregnant or breastfeeding

ask a health professional before use.

Keep out of reach of children

Do not use on infants. If swallowed, get medical help or contact a Poison Control Center (1-800-222-1222) right away.

Directions

Adults and children 12 years of age and over: Carefully remove backing from patch. Apply sticky side of patch to affected area. Wear one patch up to 8 hours. Repeat as necessary, but no more than 3 times daily. Discard patch after single use. Reseal pouch after opening. Children under 12 years of age: consult a physician.

Other Information

Store at room temperature, not to exceed 86'F (30'C).

Inactive Ingredients

carboxymethylcellulose sodium, dihydroxyaluminum aminoacetate, glycerin, iodopropynyl butylcarbamate, kaolin, mineral oil, petrolatum, phenoxyethanol, polyacrylic acid, polysorbate 80, povidone, propylene glycol, sodium polyacrylate, tartaric acid, titanium dioxide, water, 3-(2-ethylhexyloxy)propane-1,2-diol